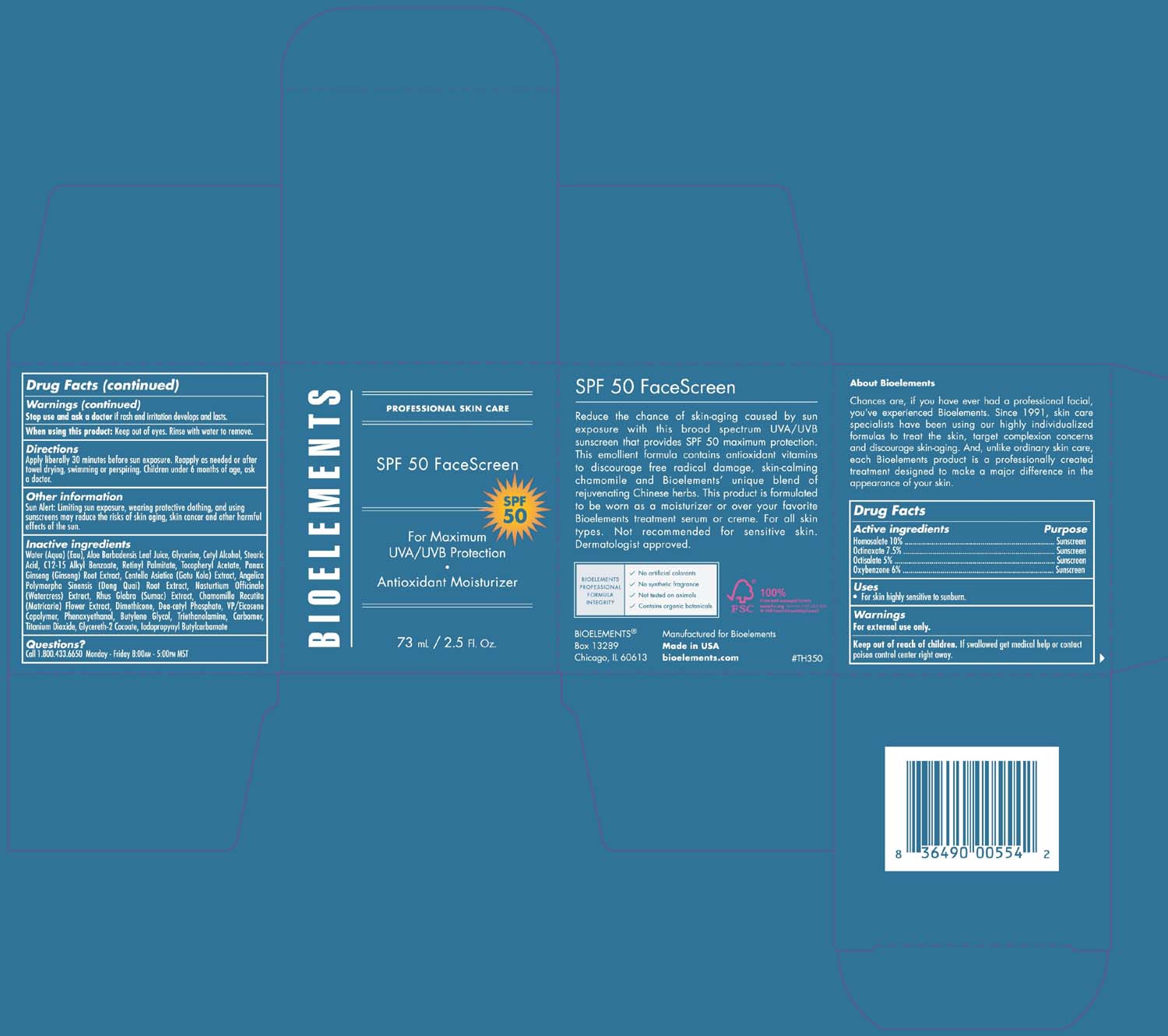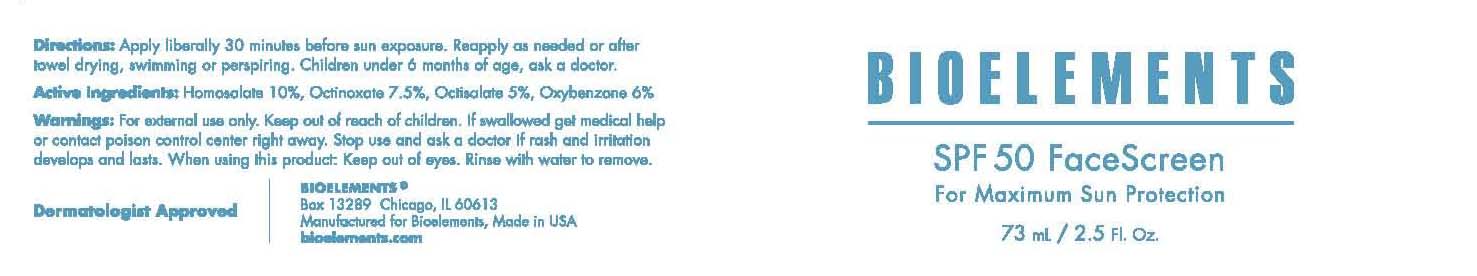 DRUG LABEL: Bioelements, Inc. 
NDC: 49825-117 | Form: CREAM
Manufacturer: Bioelements, Inc.
Category: otc | Type: HUMAN OTC DRUG LABEL
Date: 20120117

ACTIVE INGREDIENTS: HOMOSALATE 10 mL/100 mL; OCTINOXATE 7.5 mL/100 mL; OCTISALATE 5 mL/100 mL; OXYBENZONE 6 mL/100 mL
INACTIVE INGREDIENTS: WATER; ALOE; GLYCERIN; CETYL ALCOHOL; STEARIC ACID; ALKYL (C12-15) BENZOATE; VITAMIN A PALMITATE; .ALPHA.-TOCOPHEROL ACETATE; ASIAN GINSENG; CENTELLA ASIATICA; ANGELICA SINENSIS ROOT; RORIPPA NASTURTIUM-AQUATICUM; RHUS GLABRA BARK; CHAMOMILE; DIMETHICONE; DIETHANOLAMINE CETYL PHOSPHATE; PHENOXYETHANOL; BUTYLENE GLYCOL; TROLAMINE; CARBOMER 934; TITANIUM DIOXIDE; GLYCERETH-2 COCOATE; IODOPROPYNYL BUTYLCARBAMATE

SPF 50 FaceScreen

Active Ingredients Purpose

Homosalate 10% Sunscreen

Octinoxate 7.5% Sunscreen

Octisalate 5% Sunscreen

Oxybenzone 6% Sunscreen

Warnings

For external use only.

Keep out of reach of children. If swallowed get medical help or contact poison control center right away.

Stop use and ask a doctor if rash and irritation develops and lasts

When using this product: keep out of eyes. Rinse with water to remove.

Uses:

for skin highly sensitive to sunburn

Directions:

Apply liberally 30 minutes before sun exposure. Reapply as needed or after towel drying, swimming or perspiring. Children under 6 months of age, ask a doctor.

INACTIVE INGREDIENT

Water (Aqua) (Eau), Aloe Barbadensis Leaf Juice, Glycerine, Cetyl Alcohol, Stearic Acid, C12-15 Alkyl Benzoate, Retinyl Palmitate, Tocopheryl Acetate, Panax Ginseng (Ginseng) Root Extract, Centella Asiatica (Gatu Kola) Extract, Angelica Polymorpha Sinensis (Dong Quai) Root Extract, Nasturtium Officinale (Watercress) Extract, Rhus Glabra (Sumac) Extract, Chamomilla Recutita (Matricaria) Flower Extract, Dimethicone, Dea-cetyl Phosphate, VP/Eicosene Copolymer, Phenoxyethanol, Butylene Glycol, Triethanolamine, Carbomer, Titanium Dioxide, Glycereth-2 Cocoate, Iodopropynyl Butylcarbamate

PACKAGE LABEL

Bioelements

SPF 50

for Maximum UVA/UVB Protection

Antioxidant Moisturizer

73 mL/2.5 Fl. Oz.